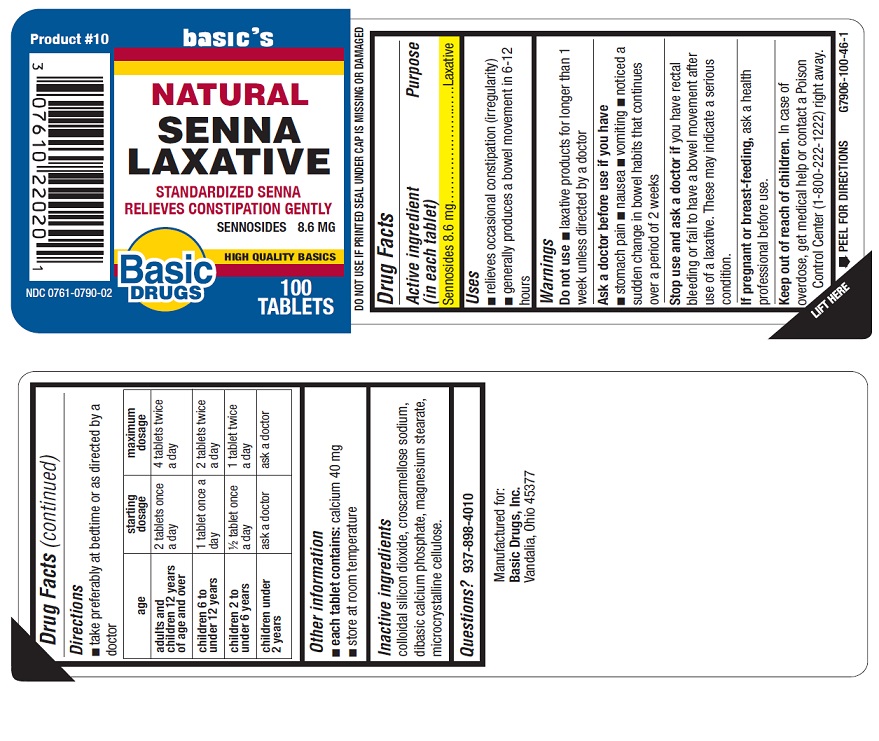 DRUG LABEL: NATURAL SENNA LAXATIVE
NDC: 0761-0790 | Form: TABLET
Manufacturer: Basic Drugs, Inc.
Category: otc | Type: HUMAN OTC DRUG LABEL
Date: 20240912

ACTIVE INGREDIENTS: SENNOSIDES 8.6 mg/1 1
INACTIVE INGREDIENTS: SILICON DIOXIDE; CROSCARMELLOSE SODIUM; ANHYDROUS DIBASIC CALCIUM PHOSPHATE; MAGNESIUM STEARATE; MICROCRYSTALLINE CELLULOSE

BASIC DRUGS - NATURAL SENNA LAXATIVE - SENNOSIDES 8.6MG (0761-0790)

Active ingredient (in each tablet)

SENNOSIDES 8.6MG

Purpose

LAXATIVE

Uses

- for the relief of occasional constipation
- generally causes bowel movement in 6 to 12 hours

Warnings

Do not use laxative products when abdominal pain, nausea, or vomiting are present unless directed by a doctor.

Ask a doctor before use if you have

- noticed a sudden change in bowel habits that persists over a period of 2 weeks.

Ask a doctor or pharmacist before use if you

- are taking a prescription drug. Laxatives may affect how other drugs work. Take this product 2 or more hours before or after

other drugs.

When using this product

- do not use for a period longer than 1 week.

Stop use and ask a doctor if

- rectal bleeding or failure to have a bowel movement occur after use of a laxative. These may indicate a serious condition.

If pregnant or breast-feeding, ask a health professional before use.

Keep out of reach of children.

In case of accidental overdose, get medical help or contact a Poison Control Center right away.

Directions

- take preferably at bedtime or as directed by a doctor
- If you do not have a confortable bowel movement by the second day, increase dosage by one tablet (do not exceed the maximum dosage) or decrease dose until you are confortable.

adults and children 12 years and over | - take 2 tablets once a day. - do not take more than 4 tablets twice a day.
children 6 to under 12 years | - take 1 tablet once a day. - do not take more than 2 tablets twice a day.
children 2 to under 6 years | - take 1/2 tablet once a day. - do not take more than 1 tablet twice a day.
children under 2 years | - ask a doctor

Other information

- each tablet contains: calcium 40mg
- store at room temperature

Inactive ingredients

Collodial silicon dioxide, croscarmellose sodium, dibasic calcium phosphate, magnesium stearate, microcrystalline cellulose.

Questions?

937-898-4010